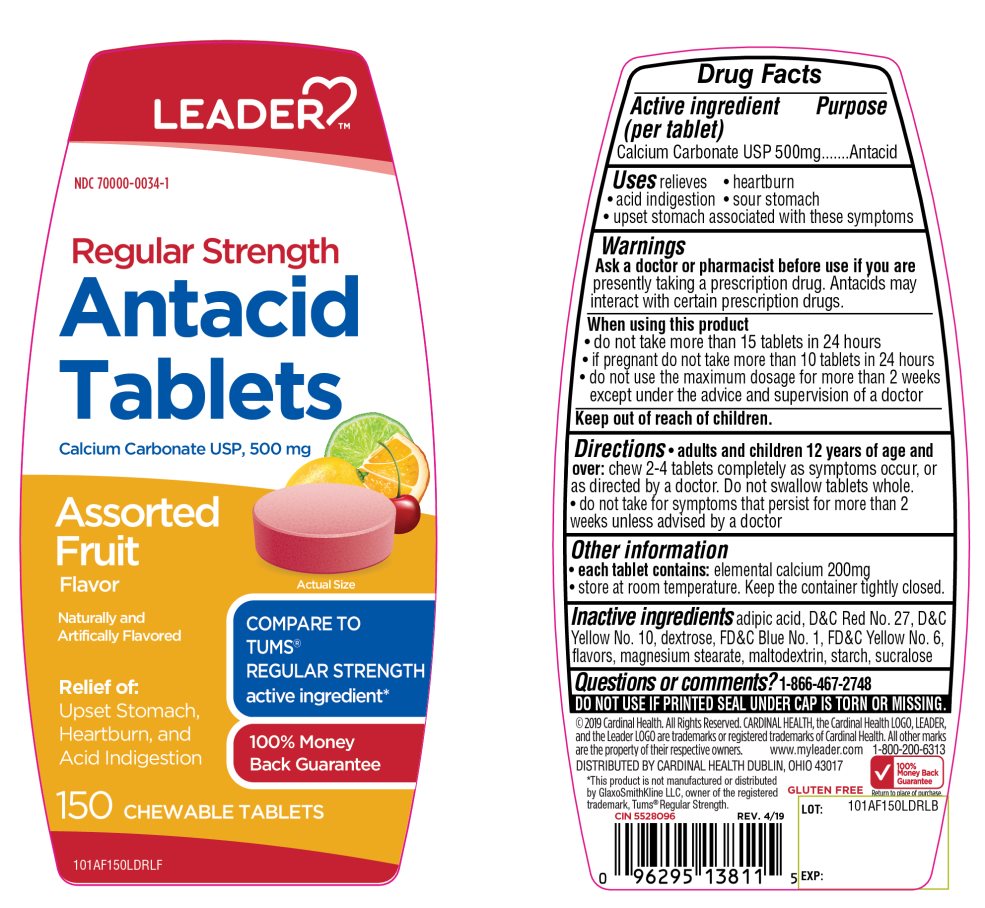 DRUG LABEL: Regular Strength Antacid

NDC: 70000-0034 | Form: TABLET, CHEWABLE
Manufacturer: CARDINAL HEALTH
Category: otc | Type: HUMAN OTC DRUG LABEL
Date: 20251014

ACTIVE INGREDIENTS: CALCIUM CARBONATE 500 mg/1 1
INACTIVE INGREDIENTS: ADIPIC ACID; D&C RED NO. 27; D&C YELLOW NO. 10; DEXTROSE, UNSPECIFIED FORM; FD&C BLUE NO. 1; FD&C YELLOW NO. 6; MAGNESIUM STEARATE; MALTODEXTRIN; STARCH, CORN; SUCRALOSE

Regular Strength Antacid Tablets Assorted Fruit Flavor

Active ingredient

Calcium Carbonate USP 500mg

Purpose

Antacid

Uses

relieves:

- heartburn
- sour stomach
- acid indigestion
- upset stomach associated with these symptoms

Warnings

Ask a doctor or pharmacist before use if you aretaking a prescription drug. Antacids may interact with certain prescription drugs.

When using this product

- do not take more than 15 tablets in 24 hours
- if pregnant do not take more than 10 tablets in 24 hours
- do not use the maximum dosage for more than 2 weeks except under the advice and supervision of a doctor.

Directions

- Adults and children 12 years of age and over:Chew 2-4 tablets completely as symptoms occur, or as directed by a doctor. Do not swallow tablets whole.
- Do not take for symptoms that persist for more than 2 weeks unless advised by a doctor.

Other Information

- each tablets contains:elemental calcium 200mg
- Store at room temperature. Keep the container tightly closed

SAFETY SEALED: DO NOT USE IF PRINTED SEAL UNDER CAP IS TORN OR MISSING

Inactive ingredients

adipic acid, D&C Red No. 27, D&C Yellow No. 10, dextrose, FD&C Blue No. 1, flavors, magnesium stearate, maltodextrin, starch, sucralose.

Package/Label Principal Display Panel

NDC 70000-0034-1

COMPARE TO TUMS® REGULAR STRENGTH active ingredient*

Regular Strength

Antacid Tablets

Calcium Carbonate 500mg

Assorted Fruit Flavor

Naturally and Artificially Flavored

Relieves:

Upset Stomach

Heartburn

Acid Indigestion

100% Money Back Guarantee

150 Chewable Tablets

©2019 Cardinal Health. All Rights Reserved. CARDINAL HEALTH, the Cardinal Health LOGO, LEADER, and the Leader LOGO are trademarks or registered trademarks of Cardinals Health.

All other marks are the property of their respective owners.

www.myleader.com

DISTRIBUTED BY CARDINAL HEALTH DUBLIN, OHIO 43017

*This product is not manufactured or distributed by GlaxoSmithKline LLC, owner of the registered trademark, Tums®Regular Strength.